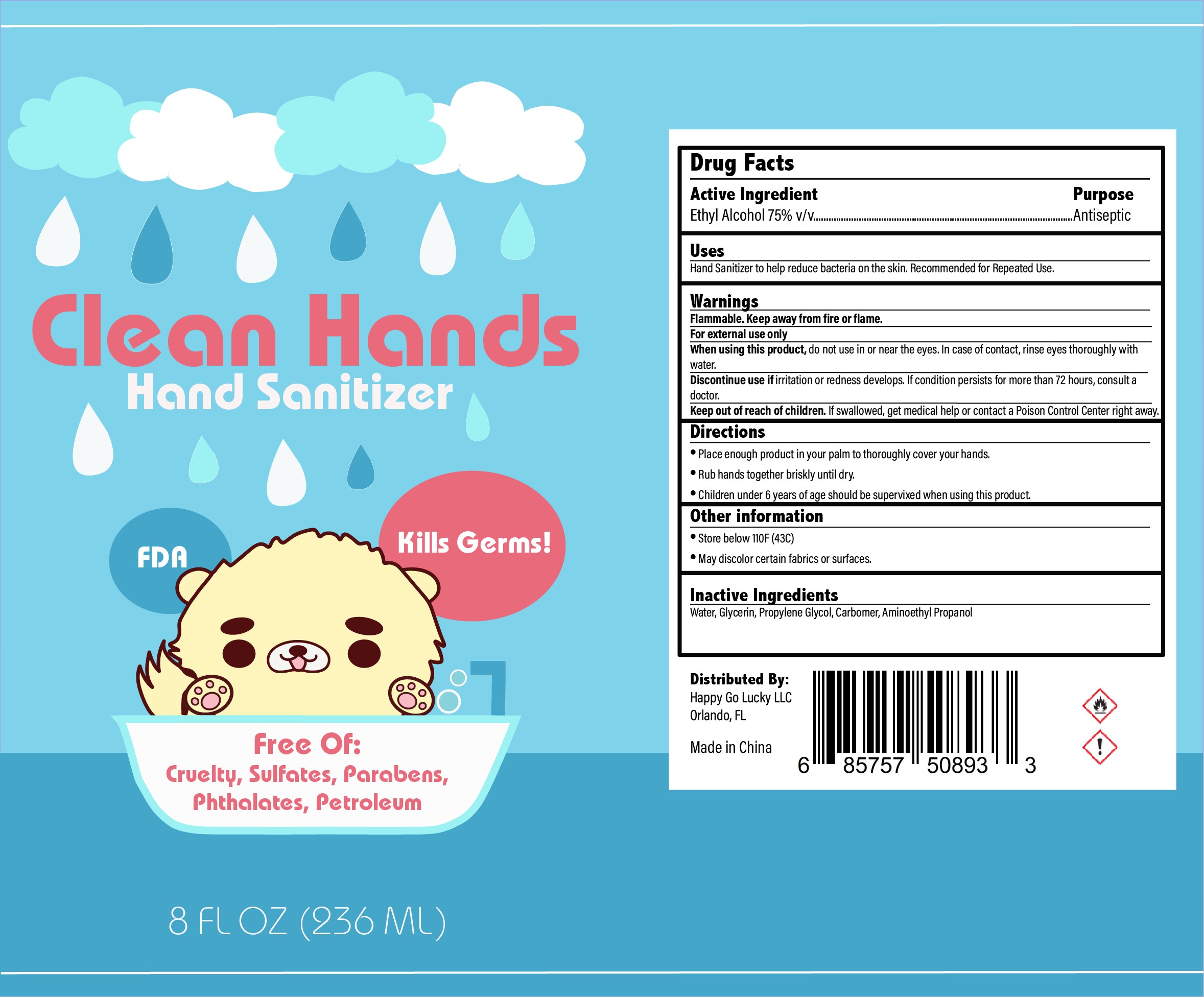 DRUG LABEL: Clean Hands
NDC: 79044-111 | Form: LIQUID
Manufacturer: Happy Go Lucky LLC
Category: otc | Type: HUMAN OTC DRUG LABEL
Date: 20200620

ACTIVE INGREDIENTS: ALCOHOL 75 mL/100 mL
INACTIVE INGREDIENTS: GLYCERIN; PROPANEDIOL; WATER; POLYACRYLIC ACID (250000 MW); AMINOMETHYLPROPANOL

Happy Go Lucky- Clean Hands Sanitizer

Active Ingredient(s)

Alcohol 75% v/v. Purpose: Antiseptic

Purpose

Antiseptic, Hand Sanitizer

Use

Hand Sanitizer to help reduce bacteria that potentially can cause disease. Recommended for repeated use.

Warnings

For external use only. Flammable. Keep away from heat or flame

When using this product keep out of eyes, ears, and mouth. In case of contact with eyes, rinse eyes thoroughly with water.
Stop use and ask a doctor if irritation or rash occurs. These may be signs of a serious condition.
Keep out of reach of children. If swallowed, get medical help or contact a Poison Control Center right away.

Stop use and ask a doctor if irritation or rash occurs. These may be signs of a serious condition.

Keep out of reach of children. If swallowed, get medical help or contact a Poison Control Center right away.

Directions

- Place enough product in your palm to thoroughly cover all hands.
- Rub hands together briskly until dry.
- Supervise children under 6 years of age when using this product to avoid swallowing.

Other information

- Store below 110F (43C)
- May discolor certain fabrics or surfaces.

Inactive ingredients

glycerin, purified water, carbomer, propylene glycol, aminoethyl propanol

Package Label - Principal Display Panel

236mL NDC: 79044-111-12